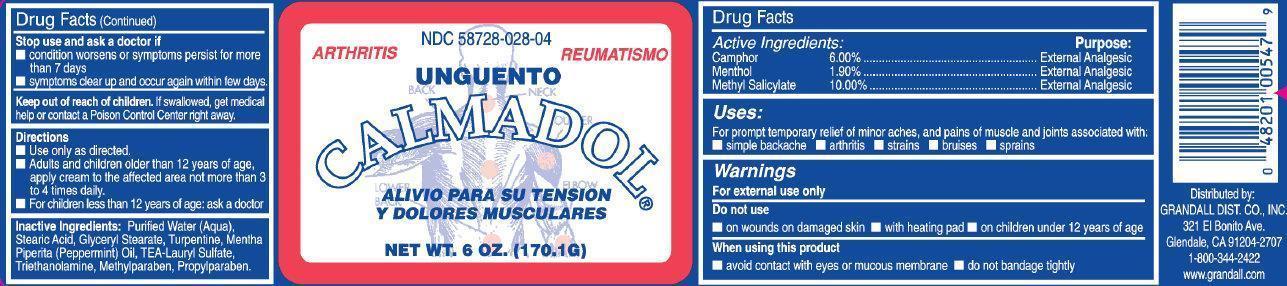 DRUG LABEL: CALMADOL
NDC: 48201-004 | Form: LINIMENT
Manufacturer: GRANDALL DISTRIBUTING, LLC
Category: otc | Type: HUMAN OTC DRUG LABEL
Date: 20251028

ACTIVE INGREDIENTS: CAMPHOR (NATURAL) 6 g/100 g; MENTHOL 1.9 g/100 g; METHYL SALICYLATE 10 g/100 g
INACTIVE INGREDIENTS: STEARIC ACID; GLYCERYL STEARATE SE; TURPENTINE; PEPPERMINT OIL; LAURYL SULFATE; TROLAMINE; METHYLPARABEN; PROPYLPARABEN

Grandall (as PLD) - CALMADOL OINTMENT (48201-004)

Drug Facts

Active Ingredients:

Camphor 6.00%

Menthol 1.90%

Methyl Salicylate 10.00%

Purpose:

External Analgesic

Uses

For prompt temporary relief of minor aches and pains of muscles and joints associated with:

- simple backache
- arthritis
- strains
- bruises
- sprains

Warnings

For external use only

When using this product

- Avoid contact with eyes and mucous membranes
- Do not bandage tightly

Stop use and ask a doctor if

- Condition worsens or symptoms persist for more than 7 days
- symptoms clear up and occur again within few days.

PREGNANCY OR BREAST FEEDING

If pregnant or breast-feeding, or if you have sensitive skin,ask a healthcare professional before use.

KEEP OUT OF REACH OF CHILDREN

Keep out of reach of childern.If swallowed, get medical help or contact a Poison Control Center immediately.

Do not use

- on wounds
- on damaged skin
- with heating pad
- on children under 12 years of age

Directions

- Use only as directed.
- Adults and chrldren older than 12 years of age, apply cream to the affected area not more than 3 to 4 trmes daily.
- For children less than 12 years of age: ask a doctor

Inactive Ingredients

Puified Water (Aqua), Stearic Acid, Glyceryl Stearate, Turpentine, Mentha Piperita (Pepperment) Oil, TEA-Lauryl Sulfate, Triethanolamine, Methylparaben, Propylparaben.

Package Labeling

ARTHRITIS

CALMADOL

NET WT. 6 oz (170.1G)